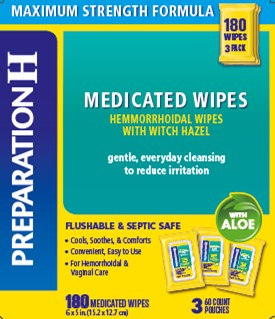 DRUG LABEL: PREPARATION H MEDICATED WIPES
NDC: 0573-0557 | Form: CLOTH
Manufacturer: Haleon US Holdings LLC
Category: otc | Type: HUMAN OTC DRUG LABEL
Date: 20240302

ACTIVE INGREDIENTS: WITCH HAZEL 5 g/1 1
INACTIVE INGREDIENTS: ALOE VERA LEAF; ANHYDROUS CITRIC ACID; COCAMIDOPROPYL BETAINE; COCAMIDOPROPYL DIMETHYLAMINE; DIAZOLIDINYL UREA; DICHLOROACETIC ACID; 3-DIMETHYLAMINOPROPYLAMINE; GLYCERIN; METHYLPARABEN; CHLOROACETIC ACID; POTASSIUM SORBATE; PROPYLENE GLYCOL; SODIUM BENZOATE; SODIUM CHLORIDE; SODIUM CITRATE, UNSPECIFIED FORM; SODIUM GLYCOLATE; WATER

Drug Facts

Active ingredient

Witch hazel 50%

Purpose

Astringent

Uses

- helps relieve the local itching and discomfort associated with hemorrhoids
- temporary relief of irritation and burning

aids in protecting irritated anorectal areas

Warnings

For external use only

When using this product

- do not exceed the recommended daily dosage unless directed by a doctor
- do not put this product into the rectum by using fingers or any mechanical device or applicator

Stop use and ask a doctor if

- bleeding occurs
- condition worsens or does not improve within 7 days

Keep out of reach of children.

If swallowed, get medical help or contact a Poison Control Center right away.

Directions

- open the lid on the top of the wipes pouch
- peel back wipes seal, remove completely and discard
- grab the top wipe at the edge of the center fold and pull out of pouch
- close lid after each use to retain moisture
- adults: unfold wipe and cleanse the area by gently wiping, patting or blotting. If necessary, repeat until all matter is removed from the area
- use up to 6 times daily or after each bowel movement and before applying topical hemorrhoidal treatments, and then discard

children under 12 years of age: consult a doctor

Other information

- for best results, flush only one or two wipes at a time

store at 20-25°C (68-77°F)

Inactive ingredients

aloe barbadensis leaf juice, anhydrous citric acid, cocamidopropyl betaine, cocamidopropyl dimethylamine, diazolidinyl urea, dichloroacetic, dimethylaminopropylamine, glycerin, methylparaben, monochloroacetic acid, potassium sorbate, propylene glycol, sodium benzoate, sodium chloride, sodium citrate, sodium glycolate, water

Questions or comments?

Call weekdays 9 AM to 5 PM EST at 1-800-99PrepHor 1-800-997-7374

Additional information

Other Uses

- for vaginal care– cleanse the area by gently wiping, patting or blotting. Repeat as needed.
- for use as a moist compress– if necessary, first cleanse the area as previously described. Fold new wipe to desired size and place in contact with tissue for a soothing and cooling effect. Leave in place for up to 15 minutes and repeat as needed.

Distributed by: GSK Consumer Healthcare, Warren, NJ 07059

For most recent product information, visit www.preparationh.com

Trademarks owned or licensed by GSK

©2022 GSK or licensor

Principal Display Panel

PREPARATIONH

Medicated Wipes

HEMORRHOIDAL WIPES

WITH WITCH HAZEL

gentle, everyday cleansing to reduce irritation

FLUSHABLE & SEPTIC SAFE

- Cools, Soothes and Comforts
- Convenient, Easy to Use
- For Hemorrhoidal and Vaginal Care

WITH ALOE

3 60 COUNT POUCHES

180 MEDICATED WIPES

6 x 5 in. (15.2 x 12.7 cm)

000077729 Front Carton